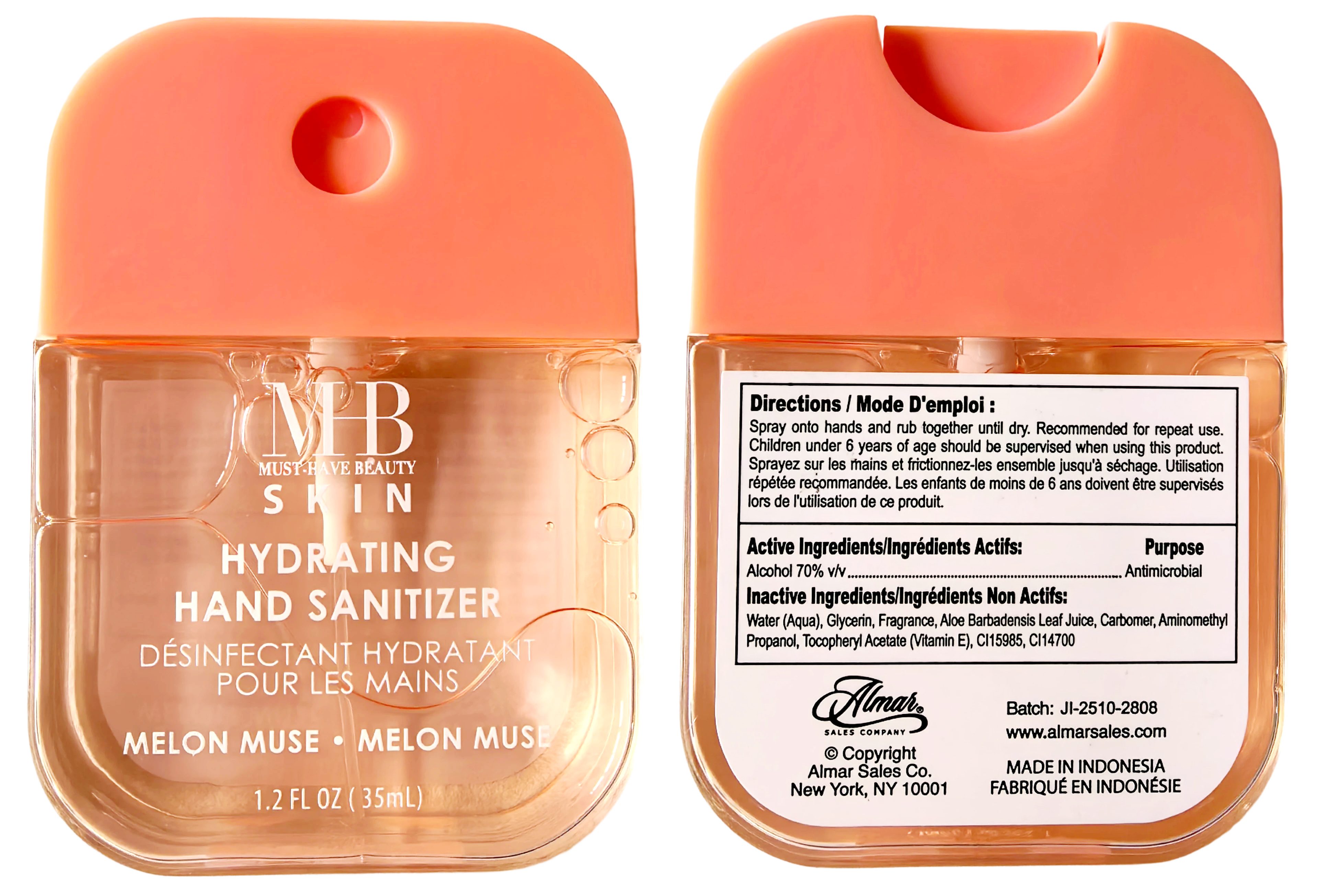 DRUG LABEL: MHB SKIN HYDRATING HAND SANITIZER, MELON MUSE
NDC: 85537-115 | Form: SPRAY
Manufacturer: PT SUPER HOME PRODUCT INDONESIA
Category: otc | Type: HUMAN OTC DRUG LABEL
Date: 20260114

ACTIVE INGREDIENTS: ALCOHOL 70 mL/100 mL
INACTIVE INGREDIENTS: CARBOMER; ALPHA-TOCOPHEROL ACETATE; ALOE VERA LEAF JUICE; CI 15985; GLYCERIN; CI 14700; FRAGRANCE 13576; AMINOMETHYLPROPANOL; AQUA

MHB SKIN HYDRATING HAND SANITIZER, MELON MUSE 35ml

Directions:

Spray onto hands and rub together until dry. Recommended for repeat use.Children under 6 years of age should be supervised when using this product.

Inactive Ingredients:

Water (Aqua), Glycerin, Fragrance, Aloe Barbadensis Leaf Juice, Carbomer, Aminomethyl Propanol, Tocophery| Acetate (Vitamin E), CI15985, CI14700

Warnings:

For external use only, Flammable, keep away from fire or flame.

When using this product

In case of contact with eyes, rinse eyes thoroughly with water. Avoid contact with broken skin.

Stop use and ask a doetor if：

Irritation and redness occurs.

Keep out of reach of children:

If swallowed, get medical help or contact a Poison Control Center.

Active Ingredients:

Ethyl Alcohol 70% v/v Purpose: Antimicrobial

Use:

Hand sanitizer helps reduce bacteria and the spread of germs